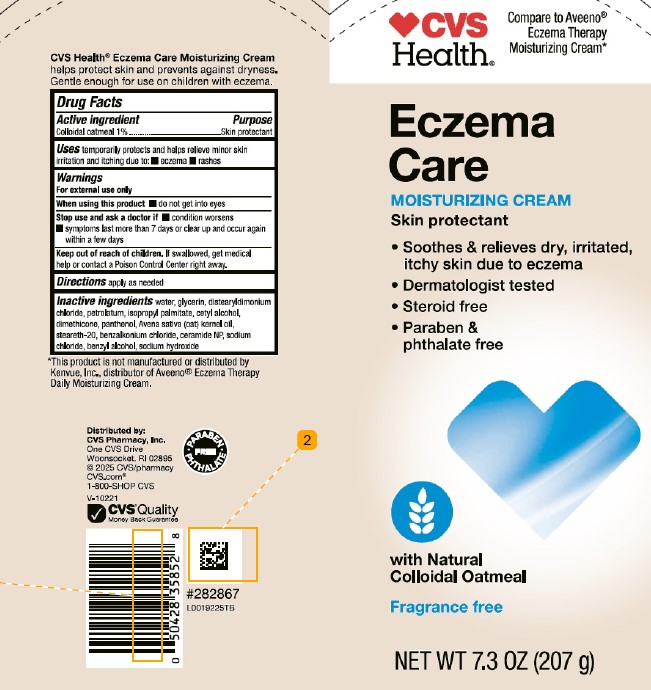 DRUG LABEL: Colloidal oatmeal
NDC: 69842-276 | Form: CREAM
Manufacturer: CVS Pharmacy, Inc.
Category: otc | Type: HUMAN OTC DRUG LABEL
Date: 20260203

ACTIVE INGREDIENTS: OATMEAL 10.4 mg/1 g
INACTIVE INGREDIENTS: WATER; GLYCERIN; DISTEARYLDIMONIUM CHLORIDE; PETROLATUM; ISOPROPYL PALMITATE; CETYL ALCOHOL; DIMETHICONE; PANTHENOL; OAT KERNEL OIL; STEARETH-20; BENZALKONIUM CHLORIDE; CERAMIDE 3; SODIUM CHLORIDE; BENZYL ALCOHOL; SODIUM HYDROXIDE

CVS 965.001/965AC
Eczema Soothing Moisturizing Cream

Claims

CVS Health®Eczema Care Moisturizing Cream helps protect skin and prevents against dryness. Gentle enough for use on children with eczema.

Active ingredient

Colloidal oatmeal 1%

Purpose

Skin protectant

Uses

temporarily protects and helps relieve minor skin irritation and itching due to:

- eczema
- rashes

Warnings

For external use only

When using this product

- do not get into eyes

Stop use and ask a doctor if

- condition worsens
- symptoms last more than 7 days or clear up and occur again within a few days

Keep out of reach of children.

If swallowed, get medical help or contact a Poison Control Center right away.

Directions

apply as needed

Inactive ingredients

water, glycerin, distearyldimonium chloride, petrolatum, isopropyl palmitate, cetyl alcohol, dimethicone, panthenol, Avena sativa (oat) kernel oil, steareth-20, benzalkonium chloride, ceramide NP, sodium chloride, benzyl alcohol, sodium hydroxide

Disclaimer

*This product is not manufactured or distributed by Kenvue, Inc., distributor of AveenoEczema Therapy Daily Moisturizing Cream.

ADVERSE REACTION

Distributed by:

CVS Pharmacy, Inc.

One CVS Drive

Woonsocket, RI 02895

©2025 CVS/pharmacy

CVS.com

1-800-SHOP CVS

CVS Quality

Money Back Guarantee

PARABEN - PHTHALATE FREE

principal Panel display

CVS HEALTH®

Compare to Aveeno®Eczema Therapy Moisturizing Cream*

Eczema

Care

MOISTURIZING CREAM

Skin protectant

- Soothes & relieves dry, irritated, itch skin due to eczema
- Dermatologist tested
- Steroid free
- Paraben & phthalate free

with Natural Colloidal Oatmeal

Fragrance free

NET WT 7.3 OZ (207 g)